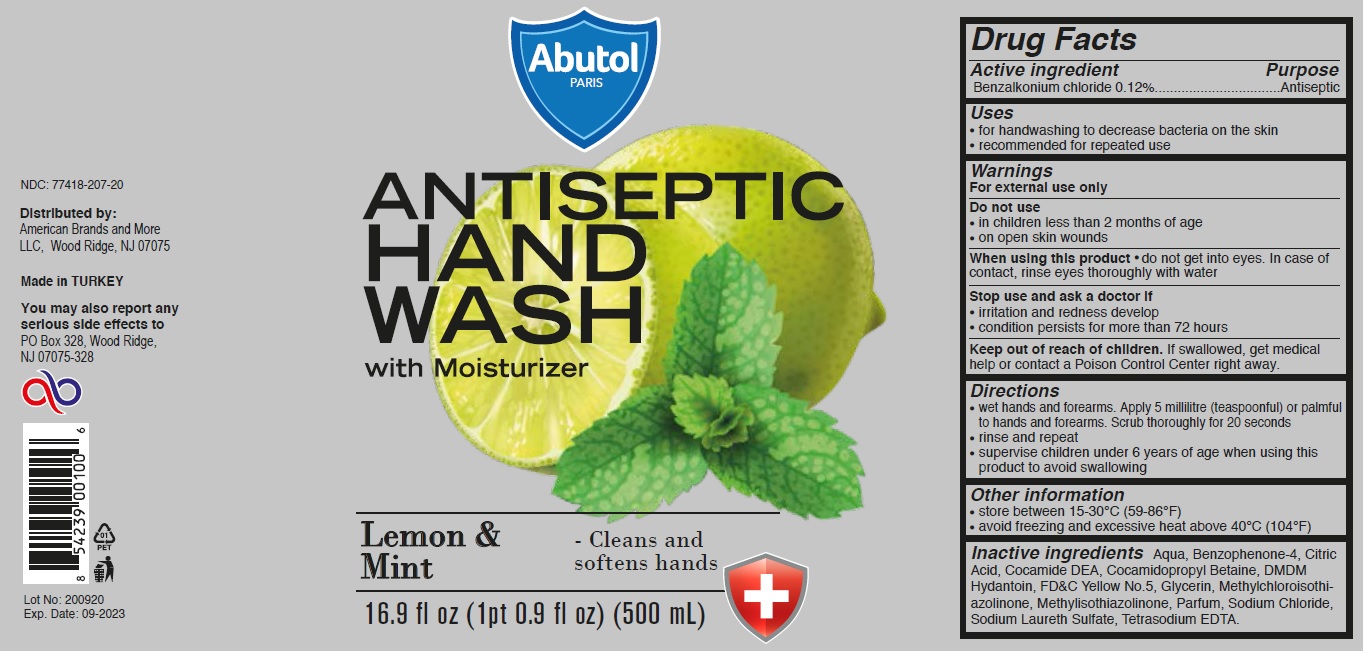 DRUG LABEL: Abutol ANTISEPTIC HAND WASH Lemon and Mint
NDC: 77418-207 | Form: LIQUID
Manufacturer: ATAK FARMA KOZMETIK VE KIMYA SANAYI TICARET ANONIM SIRKETI
Category: otc | Type: HUMAN OTC DRUG LABEL
Date: 20201103

ACTIVE INGREDIENTS: BENZALKONIUM CHLORIDE 0.12 g/100 mL
INACTIVE INGREDIENTS: WATER; SULISOBENZONE; CITRIC ACID MONOHYDRATE; COCO DIETHANOLAMIDE; COCAMIDOPROPYL BETAINE; DMDM HYDANTOIN; FD&C YELLOW NO. 5; GLYCERIN; METHYLCHLOROISOTHIAZOLINONE; METHYLISOTHIAZOLINONE; SODIUM CHLORIDE; SODIUM LAURETH-3 SULFATE; EDETATE SODIUM

Abutol PARIS ANTISEPTIC HAND WASH Lemon & Mint

Active ingredient

Benzalkonium chloride 0.12%

Purpose

Antiseptic

Uses

• for handwashing to decrease bacteria on the skin

• recommended for repeated use

Warnings

For external use only

Do not use

• in children less than 2 months of age

• on open skin wounds

When using this product • do not get into eyes. In case of contact, rinse eyes thoroughly with water

Stop use and ask a doctor if

• irritation and redness develop

• condition persists for more than 72 hours

Keep out of reach of children. If swallowed, get medical help or contact a Poison Control Center right away.

Directions

• wet hands and forearms. Apply 5 millilitre (teaspoonful) or palmful to hands and forearms. Scrub thoroughly for 20 seconds

• rinse and repeat

• supervise children under 6 years of age when using this product to avoid swallowing

Other information

• store between 15-30°C (59-86°F)

• avoid freezing and excessive heat above 40°C (104°F)

Inactive ingredients

Aqua, Benzophenone-4, Citric Acid, Cocamide DEA, Cocamidopropyl Betaine, DMDM Hydantoin, FD&C Yellow No.5, Glycerin, Methylchloroisothiazolinone, Methylisothiazolinone, Parfum, Sodium Chloride, Sodium Laureth Sulfate, Tetrasodium EDTA.

Abutol PARIS

with Moisturizer

Lemon & Mint - Cleans and soften hands

Distributed by:

American Brands and More

LLC, Wood Ridge, NJ 07075

Made in TURKEY

You may also report any serious side effects to

PO Box 328, Wood Ridge, NJ 07075-328